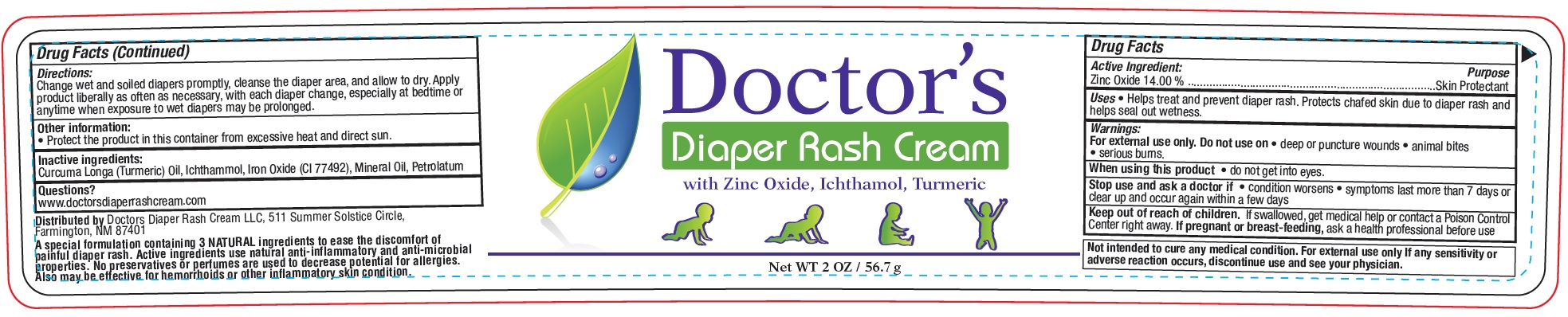 DRUG LABEL: Doctors Diaper Rash Cream
NDC: 83432-402 | Form: CREAM
Manufacturer: DOCTOR'S DIAPER RASH CREAM, INC
Category: otc | Type: HUMAN OTC DRUG LABEL
Date: 20231106

ACTIVE INGREDIENTS: ZINC OXIDE 140 mg/1 g
INACTIVE INGREDIENTS: TURMERIC; ICHTHAMMOL; FERRIC OXIDE YELLOW; MINERAL OIL; PETROLATUM

Doctor's Diaper Rash Cream

Active Ingredient:

Zinc Oxide 14.00 %

Purpose

Skin Protectant

Uses

• Helps treat and prevent diaper rash. Protects chafed skin due to diaper rash and helps seal out wetness.

Warnings:

For external use only.

Do not use on

• deep or puncture wounds • animal bites • serious burns.

When using this product

• do not get into eyes.

Stop use and ask a doctor if

• condition worsens • symptoms last more than 7 days or clear up and occur again within a few days

Keep out of reach of children.

If swallowed, get medical help or contact a Poison Control Center right away.

If pregnant or breast-feeding,

ask a health professional before use

Not intended to cure any medical condition. For external use only If any sensitivity or adverse reaction occurs, discontinue use and see your physician.

Directions:

Change wet and soiled diapers promptly, cleanse the diaper area, and allow to dry. Apply product liberally as often as necessary, with each diaper change, especially at bedtime or anytime when exposure to wet diapers may be prolonged.

Other information:

• Protect the product in this container from excessive heat and direct sun.

Inactive ingredients:

Curcuma Longa (Turmeric) Oil, Ichthammol, Iron Oxide (CI 77492), Mineral Oil, Petrolatum

Questions?

www.doctorsdiaperrashcream.com